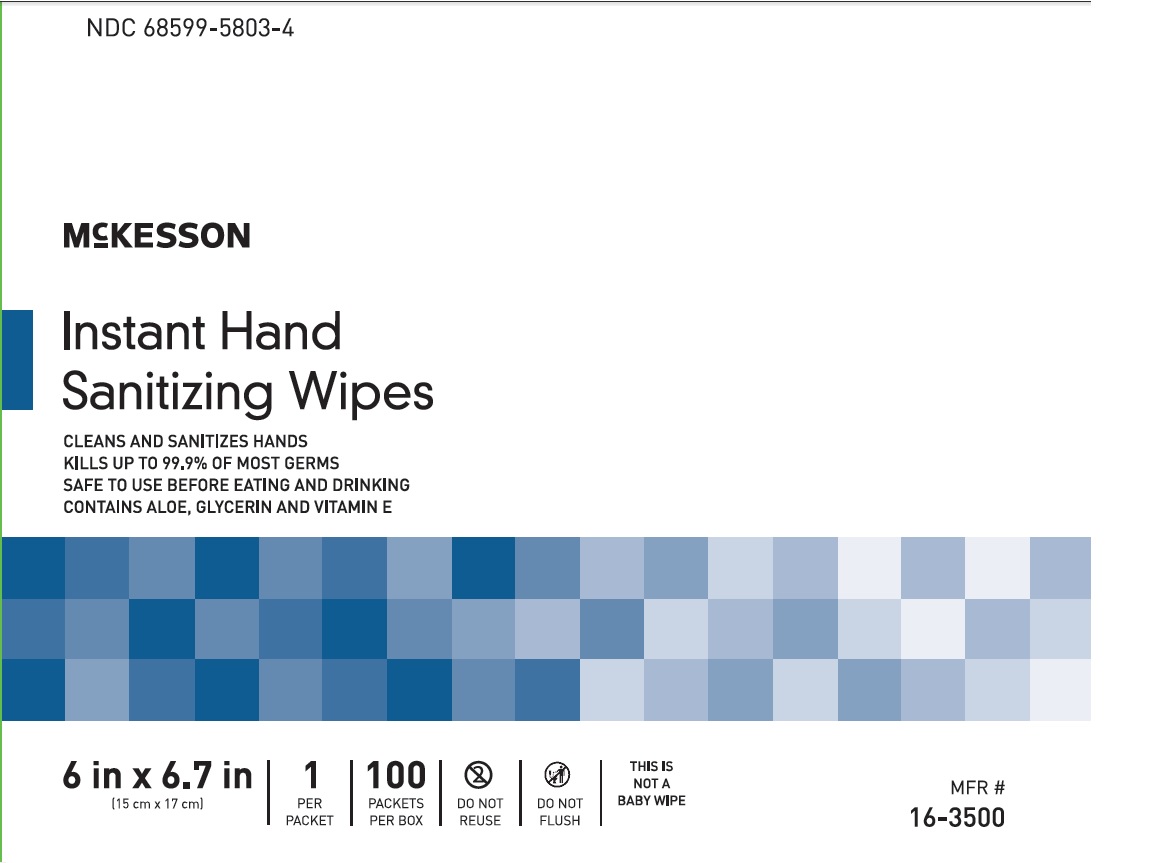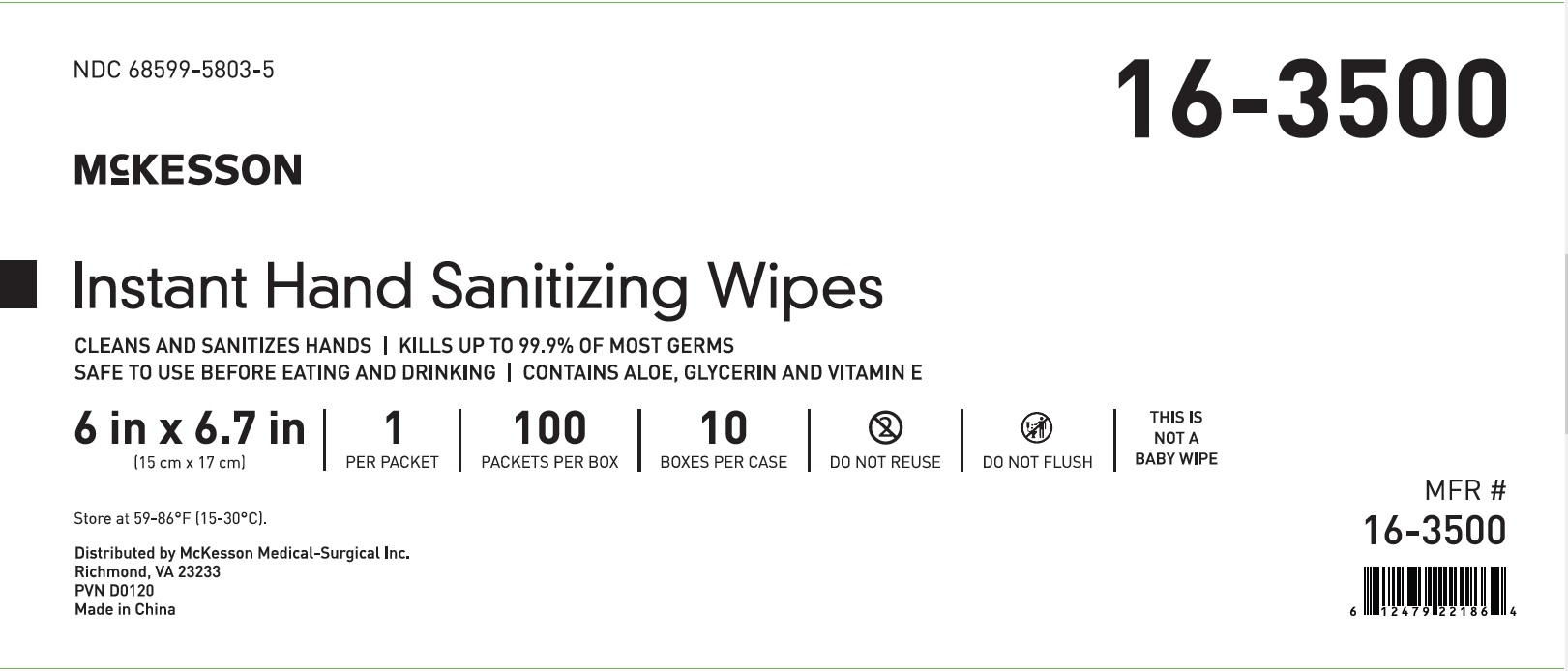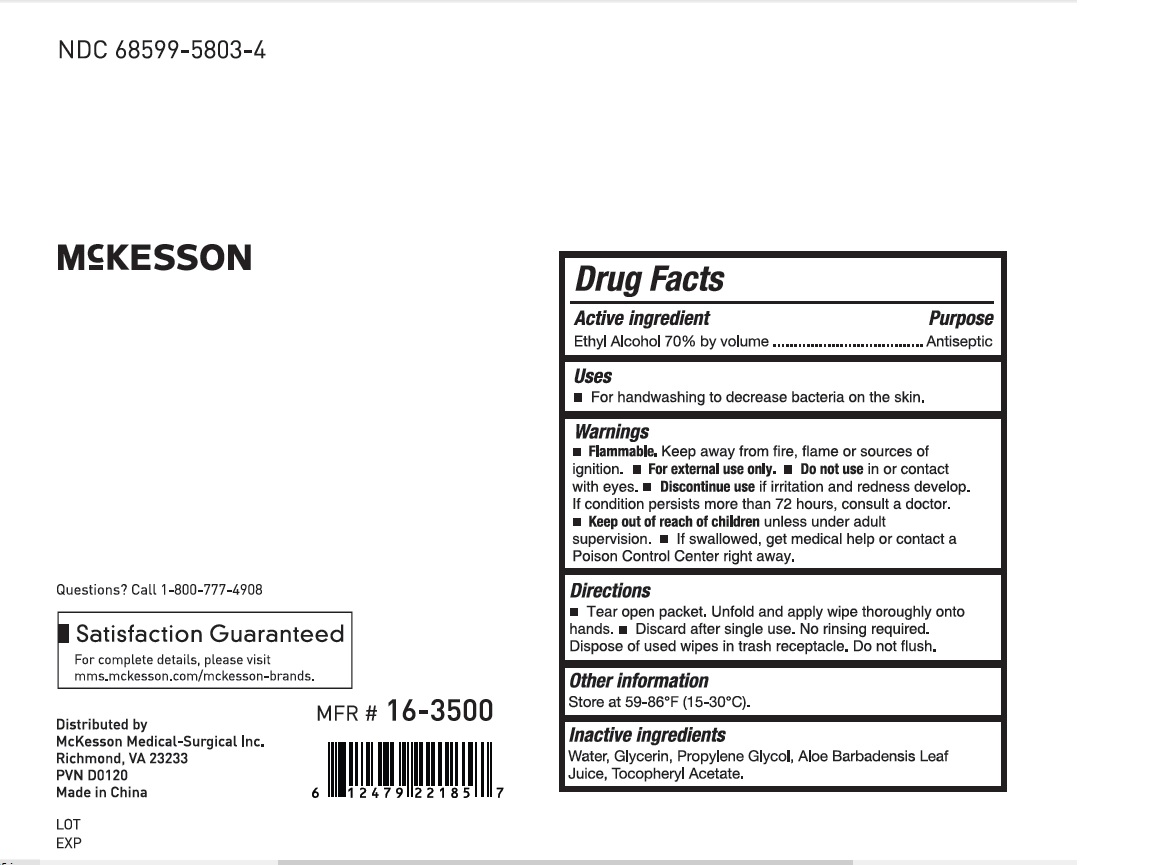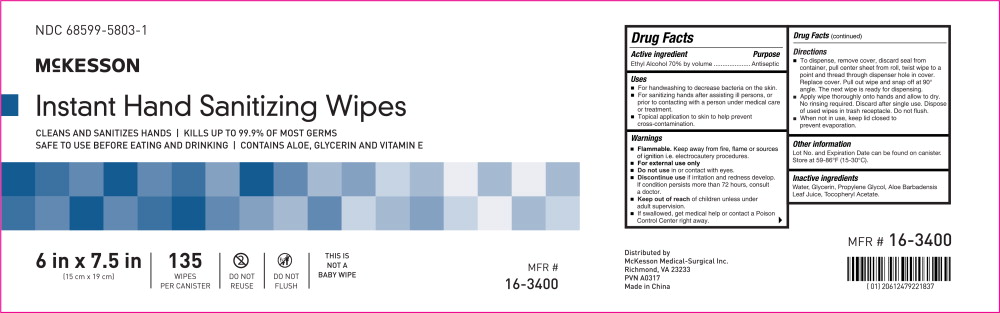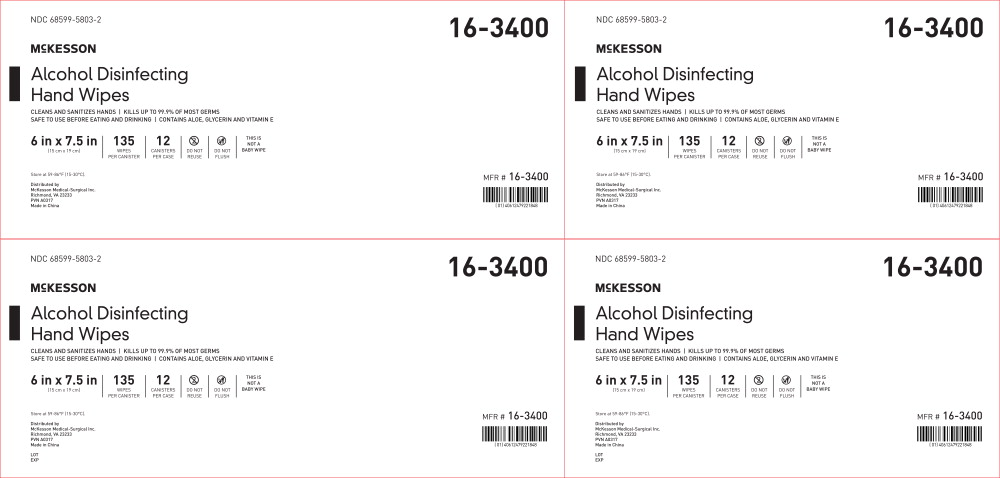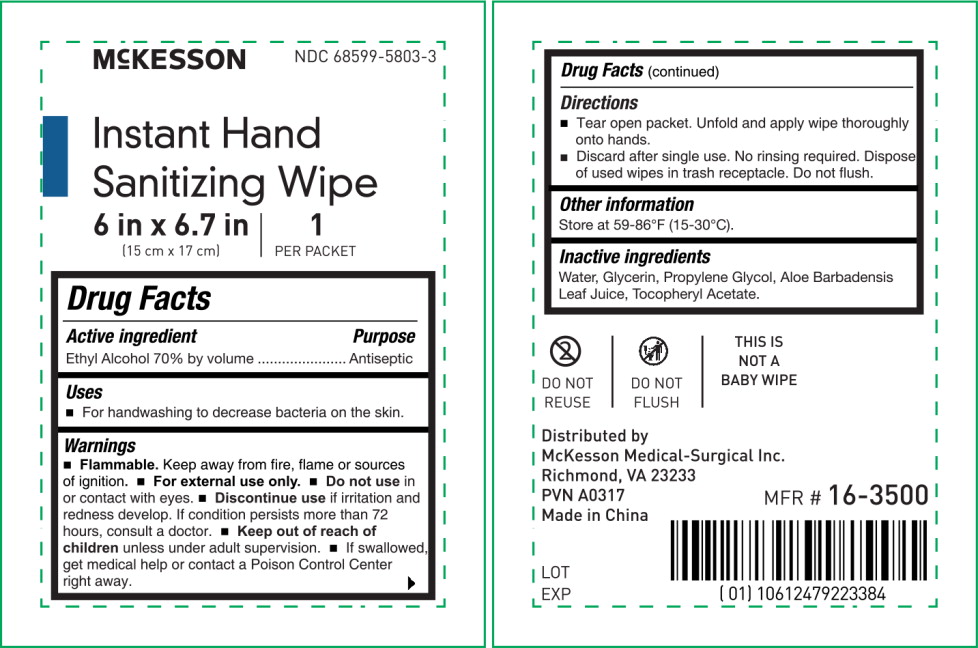 DRUG LABEL: Alcohol Disinfecting Wipe
NDC: 68599-5803 | Form: SWAB
Manufacturer: McKesson Medical-Surgical
Category: otc | Type: HUMAN OTC DRUG LABEL
Date: 20241011

ACTIVE INGREDIENTS: ALCOHOL 70 mL/1 1
INACTIVE INGREDIENTS: WATER; GLYCERIN; PROPYLENE GLYCOL; ALOE; .ALPHA.-TOCOPHEROL ACETATE

Drug Facts

Active ingredient

Ethyl Alcohol 70% by volume

Purpose

Antiseptic

Uses

- For handwashing to decrease bacteria on the skin.

Warnings

- Flammable.Keep away from fire, flame or sources of ignition.
- For external use only.

- Do not usein or contact with eyes.
- Discontinue useif irritation and redness develop. If condition persists more than 72 hours, consult a doctor.

KEEP OUT OF REACH OF CHILDREN

- Keep out of reach of childrenunless under adult supervision.
- If swallowed, get medical help or contact a Poison Control Center right away.

Directions

- Tear open packet. Unfold and apply wipe thoroughly onto hands.
- Discard after single use. No rinsing required. Dispose of used wipes in trash receptacle. Do not flush.

Other information

Store at 59-86° (15-30°).

Inactive ingredients

Water, Glycerin, Propylene Glycol, Aloe Barbadensis Leaf Juice, Tocopheryl Acetate.

Principal Display Panel - Canister Label

NDC 68599-5803-1

McKESSON

Instant Hand Sanitizing Wipes

CLEANS AND SANITIZES HANDS | KILLS UP TO 99.9% OF MOST GERMS

SAFE TO USE BEFORE EATING AND DRINKING | CONTAINS ALOE, GLYCERIN AND VITAMIN E

6 in x 7.5 in

(15 cm x 19 cm)

135
WIPES
PER CANISTER

DO NOT
REUSE

DO NOT
FLUSH

THIS IS
NOT A
BABY WIPE

MFR # 16-3400

Principal Display Panel - Canister Case Label

NDC 68599-5803-2

16-3400

McKESSON

Alcohol Disinfecting
Hand Wipes

CLEANS AND SANITIZES HANDS | KILLS UP TO 99.9% OF MOST GERMS

SAFE TO USE BEFORE EATING AND DRINKING | CONTAINS ALOE, GLYERIN AND VITAMIN E

6 in x 7.5 in

(15 cm x 19 cm)

135
WIPES
PER CANISTER

12
CANISTERS
PER CASE

DO NOT REUSE

DO NOT FLUSH

THIS IS NOT A BABY WIPE

Store at 59-86°F (15-30°).

Distributed by

McKesson Medical-Surgical Inc.

Richmond, VA 23233

PVN A0317

Made in China

MFR # 16-3400

Principal Display Panel - Packet Carton Label

NDC 68599-5803-3

McKESSON

Instant Hand
Sanitizing Wipes

CLEANS AND SANITIZES HANDS

KILLS UP TO 99.9% OF MOST GERMS

SAFE TO USE BEFORE EATING AND DRINKING

CONTAINS ALOE, GLYCERIN AND VITAMIN E

6 in x 6.7 in

(15 cm x 17 cm)

1
PER
PACKET

100
PACKETS
PER BOX

DO NOT
REUSE

DO NOT
FLUSH

THIS IS
NOT A
BABY WIPE

MFR #
16-3500

Principal Display Panel - Packet Case Label

NDC 68599-5803-4

McKESSON

Instant Hand Sanitizing Wipes

CLEANS AND SANITIZES HANDS | KILLS UP TO 99.9% OF MOST GERMS

SAFE TO USE BEFORE EATING AND DRINKING | CONTAINS ALOE, GLYCERIN AND VITAMIN E

6 in x 6.7 in

(15 cm x 17 cm)

1PER PACKET

100PACKETS PER BOX

10BOXES PER CASE

DO NOT REUSE

DO NOT FLUSH

THIS IS NOT A BABY WIPE

Store at 59-86°F (15-30°C).

Distributed by McKesson Medical-Surgical Inc.

Richmond, VA 23233

PVN A0317

Made in China

MFR # 16-3500

Principal Display Panel - Packet Label

McKESSONNDC 68599-5803-5

Instant Hand Sanitizing Wipe

6 in x 6.7 in

(15 cm x 17 cm)

1PER PACKET